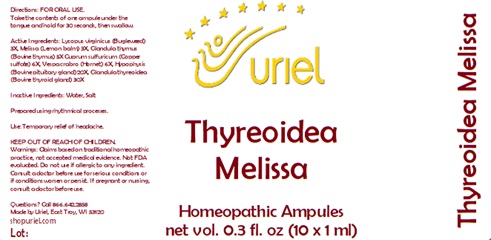 DRUG LABEL: Thyreoidea Melissa
NDC: 48951-9014 | Form: LIQUID
Manufacturer: Uriel Pharmacy Inc.
Category: homeopathic | Type: HUMAN OTC DRUG LABEL
Date: 20241206

ACTIVE INGREDIENTS: FUCUS VESICULOSUS 3 [hp_X]/1 mL; LYCOPUS VIRGINICUS 3 [hp_X]/1 mL; MELISSA OFFICINALIS 3 [hp_X]/1 mL; BOS TAURUS THYMUS 5 [hp_X]/1 mL; ARSENIC TRIOXIDE 6 [hp_X]/1 mL; CUPRIC SULFATE 6 [hp_X]/1 mL; VESPA CRABRO 6 [hp_X]/1 mL; BOS TAURUS PITUITARY GLAND 20 [hp_X]/1 mL; THYROID, UNSPECIFIED 30 [hp_X]/1 mL
INACTIVE INGREDIENTS: WATER; SODIUM CHLORIDE

Thyreoidea Melissa

INDICATIONS AND USAGE

Directions: FOR ORAL USE.

DOSAGE AND ADMINISTRATION

Take the contents of one ampule under the tongue and hold for 30 seconds, then swallow.

ACTIVE INGREDIENT

Active Ingredients: Lycopus virginicus (Bugleweed) 3X, Melissa (Lemon balm) 3X, Glandula thymus (Bovine thymus) 5X Cuprum sulfuricum (Copper sulfate) 6X, Vespa crabro (Hornet) 6X, Hypophysis (Bovine pituitary gland) 20X, Glandula thyreoidea (Bovine thyroid gland) 30X

Inactive Ingredients: Water, Salt

Prepared using rhythmical processes.

PURPOSE

Use: Temporary relief of headache.

KEEP OUT OF REACH OF CHILDREN.

WARNINGS

Warnings: Claims based on traditional homeopathic practice, not accepted medical evidence. Not FDA evaluated. Do not use if allergic to any ingredient. Consult a doctor before use for serious conditions or if conditions worsen or persist. If pregnant or nursing, consult a doctor before use.

QUESTIONS

Questions? Call 866.642.2858 Uriel, East Troy, WI 53120 shopuriel.com